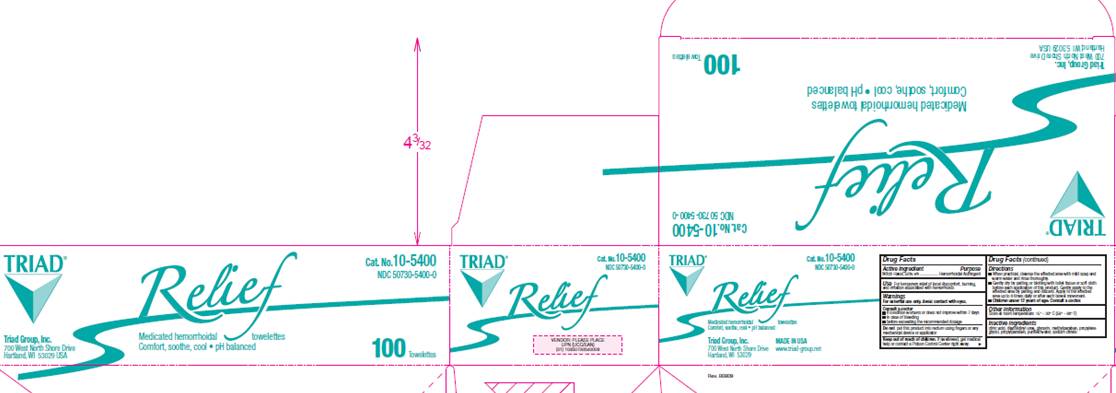 DRUG LABEL: Relief Towelette
NDC: 50730-5400 | Form: SOLUTION
Manufacturer: H and P Industries, Inc. dba Triad Group
Category: otc | Type: HUMAN OTC DRUG LABEL
Date: 20091202

ACTIVE INGREDIENTS: witch hazel .5 mL/1 1
INACTIVE INGREDIENTS: citric acid monohydrate; diazolidinylurea; glycerin; methylparaben; propylene glycol; propylparaben; sodium citrate; water

Drug Facts

Active ingredient

Witch Hazel 50%

Purpose

Astringent

Use

For temporary relief of local discomfort, burning, and irritation associated with hemorrhoids.

Warnings

For external use only.
Avoid contact with eyes.

Do not

put this product into the rectum using fingers or any mechanical device or applicator.

Stop use and ask a doctor

- if condition worsens or does not improve within 7 days
- in case of bleeding
- before exceeding the recommended dosage.

Keep out of reach of children

If swallowed, get medical help or contact a Poison Control Center right away.

Directions

- When practical, cleanse the affected area with mild soap and warm water and rinse thoroughly.
- Gently dry by patting or blotting with toilet tissue or soft cloth before each application of this product. Gently apply to the affected area by patting and then discard. Apply to the affected area up to 6 times daily or after each bowel movement.
- Children under 12 years of age: consult a doctor.

Other information

Store at room temperature 15° -30° C (59° - 86° F)

Inactive Ingredients

citric acid, diazolidinyl urea, glycerin, methylparaben, propylene glycol, propylparaben, sodium citrate, water

Package Information

Cat. No. 10-5400
NDC 50730-5400-0
Relief
Medicated hemorrhoidal towelettes
Comfort, soothe, cool - pH balanced
Triad Group, Inc.
700 West North Shore Drive
Hartland, WI 53029 USA
Made in USA
www.triad-group.net
100 Towelettes